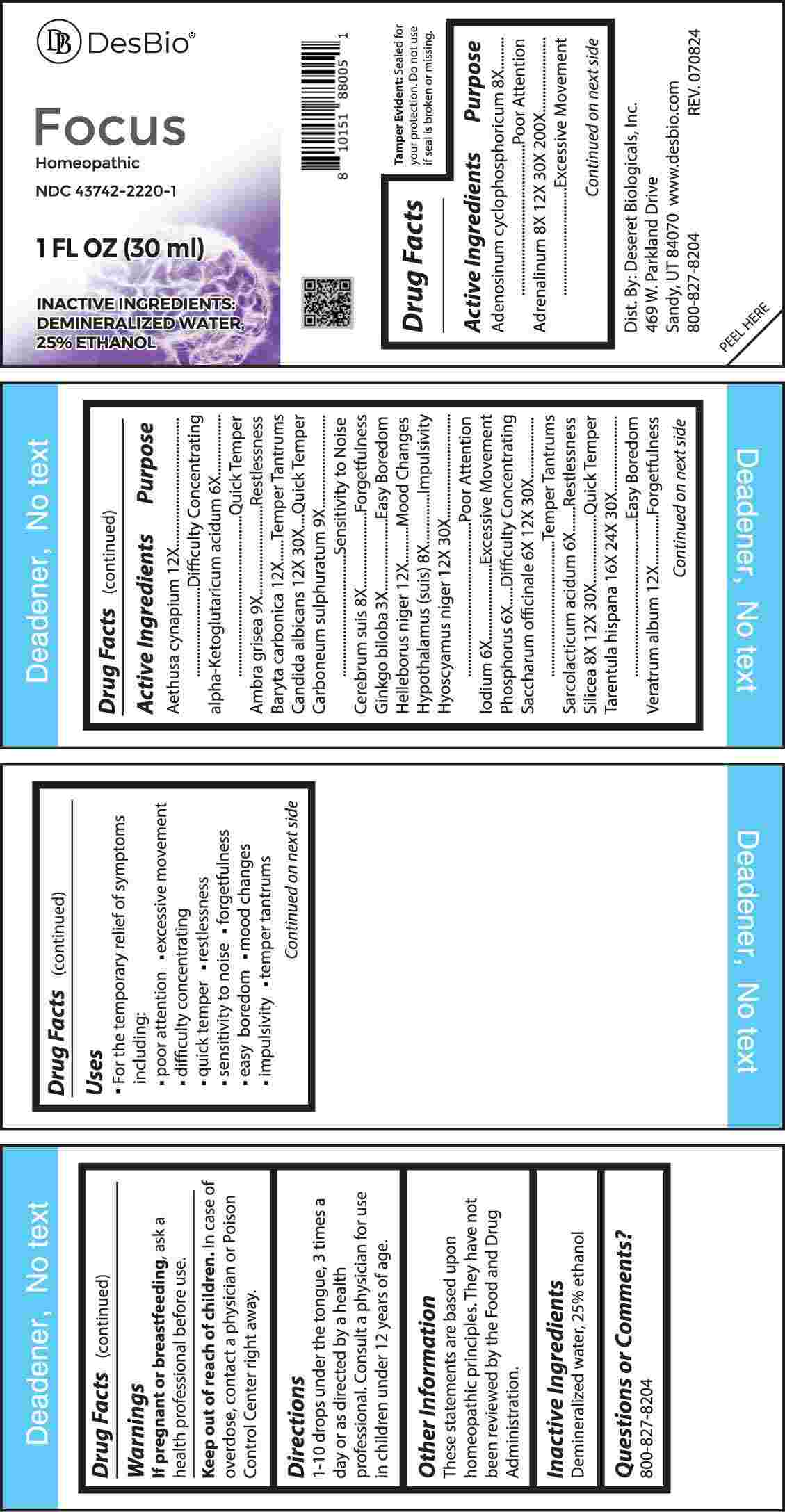 DRUG LABEL: Focus
NDC: 43742-2220 | Form: LIQUID
Manufacturer: Deseret Biologicals, Inc.
Category: homeopathic | Type: HUMAN OTC DRUG LABEL
Date: 20241113

ACTIVE INGREDIENTS: ADENOSINE CYCLIC PHOSPHATE 8 [hp_X]/1 mL; EPINEPHRINE 8 [hp_X]/1 mL; AETHUSA CYNAPIUM WHOLE 12 [hp_X]/1 mL; OXOGLURIC ACID 6 [hp_X]/1 mL; AMBERGRIS 9 [hp_X]/1 mL; BARIUM CARBONATE 12 [hp_X]/1 mL; CANDIDA ALBICANS 12 [hp_X]/1 mL; CARBON DISULFIDE 9 [hp_X]/1 mL; SUS SCROFA CEREBRUM 8 [hp_X]/1 mL; GINKGO 3 [hp_X]/1 mL; HELLEBORUS NIGER ROOT 12 [hp_X]/1 mL; SUS SCROFA HYPOTHALAMUS 8 [hp_X]/1 mL; HYOSCYAMUS NIGER 12 [hp_X]/1 mL; IODINE 6 [hp_X]/1 mL; PHOSPHORUS 6 [hp_X]/1 mL; SUCROSE 6 [hp_X]/1 mL; LACTIC ACID, L- 6 [hp_X]/1 mL; SILICON DIOXIDE 8 [hp_X]/1 mL; LYCOSA TARANTULA 16 [hp_X]/1 mL; VERATRUM ALBUM ROOT 12 [hp_X]/1 mL
INACTIVE INGREDIENTS: WATER; ALCOHOL

DRUG FACTS:

ACTIVE INGREDIENTS:

Adenosinum Cyclophosphoricum 8X, Adrenalinum 8X, 12X, 30X, 200X, Aethusa Cynapium 12X, Alpha-Ketoglutaricum Acidum 6X, Ambra Grisea 9X, Baryta Carbonica 12X, Candida Albicans 12X, 30X, Carboneum Sulphuratum 9X, Cerebrum Suis 8X, Ginkgo Biloba 3X, Helleborus Niger 12X, Hypothalamus (Suis) 8X, Hyoscyamus Niger 12X, 30X, Iodium 6X, Phosphorus 6X, Saccharum Officinale 6X, 12X, 30X, Sarcolacticum Acid 6X, Silicea 8X, 12X, 30X, Tarentula Hispana 16X, 24X, 30X, Veratrum Album 12X.

PURPOSE:

Adenosinum Cyclophosphoricum – Poor Attention, Adrenalinum – Excessive Movement, Aethusa Cynapium – Difficulty Concentrating, Alpha-Ketoglutaricum Acidum – Quick Temper, Ambra Grisea - Restlessness, Baryta Carbonica – Temper Tantrums, Candida Albicans – Quick Temper, Carboneum Sulphuratum – Sensitivity to Noise, Cerebrum Suis - Forgetfulness, Ginkgo Biloba – Easy Boredom, Helleborus Niger – Mood Changes, Hypothalamus Suis - Impulsivity, Hyoscyamus Niger – Poor Attention, Iodium – Excessive Movement, Phosphorus – Difficulty Concentrating, Saccharum Officinale – Temper Tantrums, Sarcolacticum Acid - Restlessness, Silicea – Quick Temper, Tarentula Hispana – Easy Boredom, Veratrum Album - Forgetfulness

USES:

• For the temporary relief of symptoms including:

• poor attention • excessive movement • difficult concentrating

• quick temper • restlessness • sensitivity to noise • forgetfulness

• easy boredom • mood changes • impulsivity • temper tantrums

These statements are based upon homeopathic principles. They have not been reviewed by the Food and Drug Administration.

WARNINGS:

If pregnant or breast-feeding, ask a health professional before use.

Keep out of reach of children. In case of overdose, contact a physician or Poison Control Center right away.

Tamper Evident: Sealed for your protection. Do not use if seal is broken or missing.

KEEP OUT OF REACH OF CHILDREN:

In case of overdose, contact a physician or Poison Control Center right away.

DIRECTIONS:

1-10 drops under the tongue, 3 times a day or as directed by a health professional. Consult a physician for use in children under 12 years of age.

INACTIVE INGREDIENTS:

Demineralized water, 25% ethanol

QUESTIONS:

Dist. By: Deseret Biologicals, Inc.
469 W. Parkland Drive
Sandy, UT 84070

www.desbio.com

800-827-8204

PACKAGE LABEL DISPLAY:

DesBio

Focus

Homeopathic

NDC 43742-2220-1

1 FL OZ (30 ml)